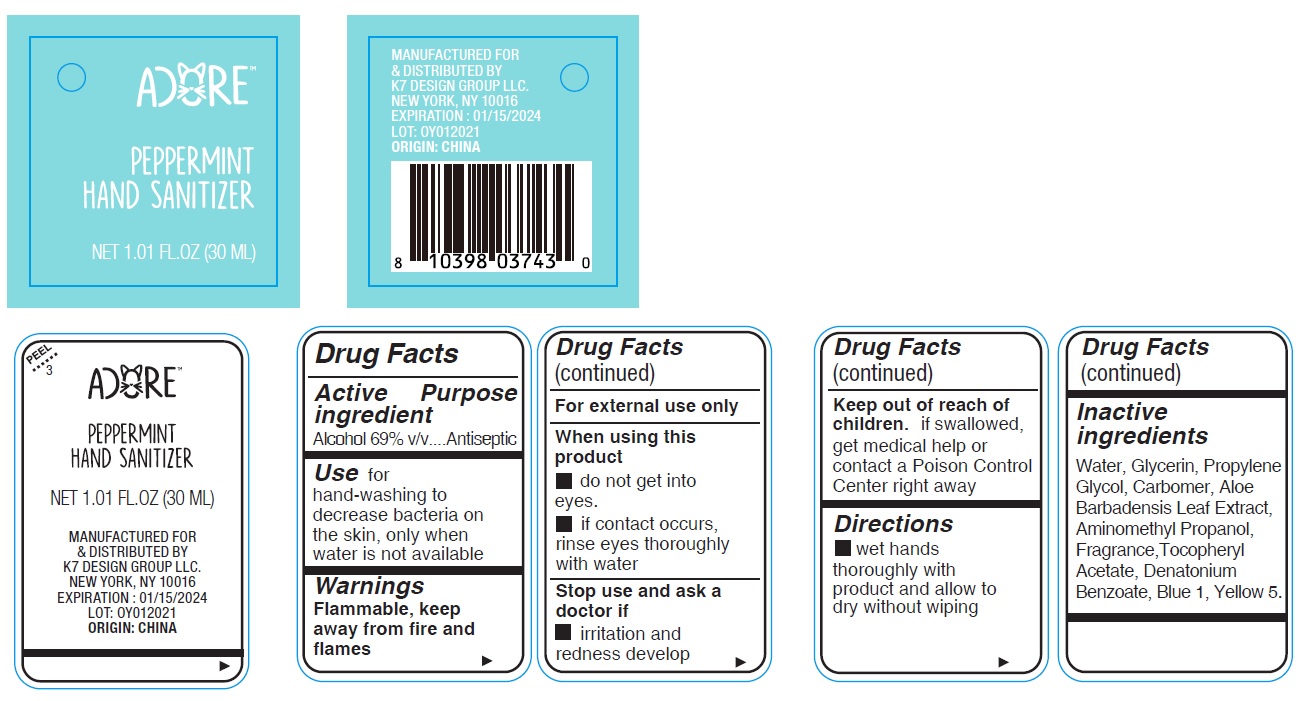 DRUG LABEL: Adore Peppermint Hand Sanitizer
NDC: 74177-989 | Form: GEL
Manufacturer: K7 Design Group Inc.
Category: otc | Type: HUMAN OTC DRUG LABEL
Date: 20210105

ACTIVE INGREDIENTS: ALCOHOL 69 mL/100 mL
INACTIVE INGREDIENTS: ALOE VERA LEAF; AMINOMETHYLPROPANOL; WATER; CARBOMER HOMOPOLYMER, UNSPECIFIED TYPE; FD&C BLUE NO. 1; DENATONIUM BENZOATE; GLYCERIN; PROPYLENE GLYCOL; .ALPHA.-TOCOPHEROL ACETATE; FD&C YELLOW NO. 5

Adore Peppermint Hand Sanitizer

Active ingredient

Alcohol 69% v/v

Purpose

Antiseptic

Use

for hand-washing to decrease bacteria on the skin, only when water is not available

Warnings

Flammable, keep away from fire and flames

For external use only

When using this product

- do not get into eyes.
- if contact occurs, rinse eyes thoroughly with water

Stop use and ask a doctor if

- irritation and redness develop

Keep out of reach of children.

if swallowed, get medical help or contact a Poison Control Center right away

Directions

- wet hands thoroughly with product and allow to dry without wiping

Inactive ingredients

Water, Glycerin, Propylene Glycol, Carbomer, Aloe Barbadensis Leaf Extract, Aminomethyl Propanol, Fragrance, Tocopheryl Acetate, Denatonium Benzoate, Blue 1, Yellow 5.

Company Information

MANUFACTURED FOR & DISTRIBUTED BY K7 DESIGN GROUP LLC

NEW YORK, NY 10016